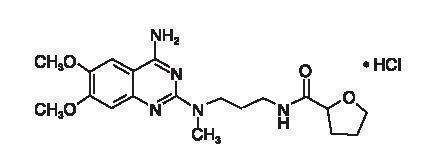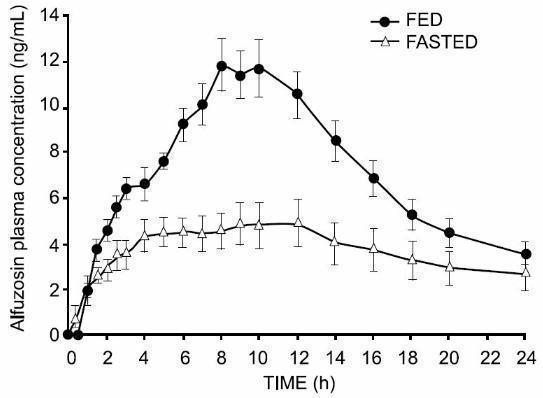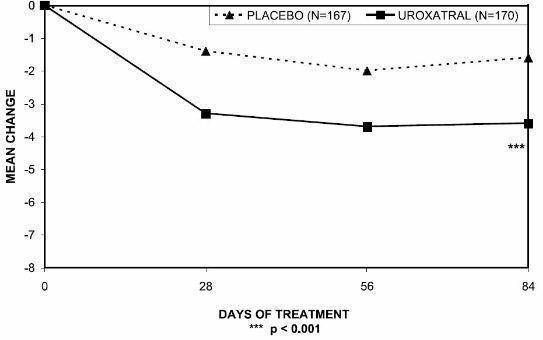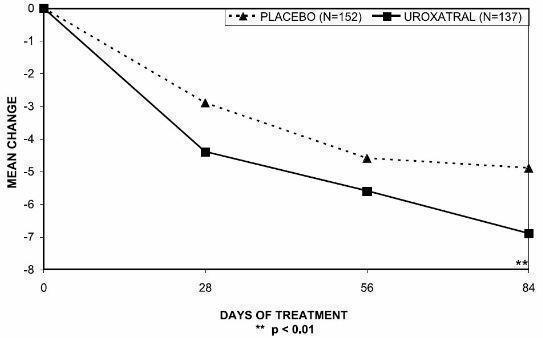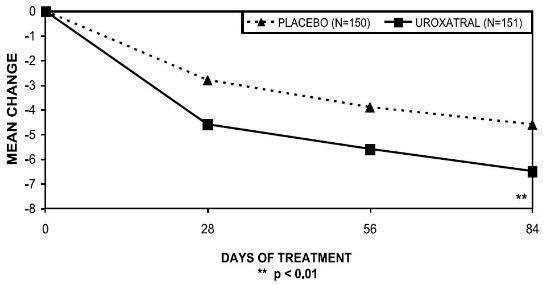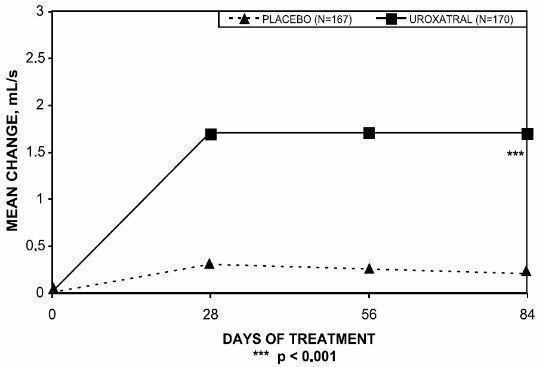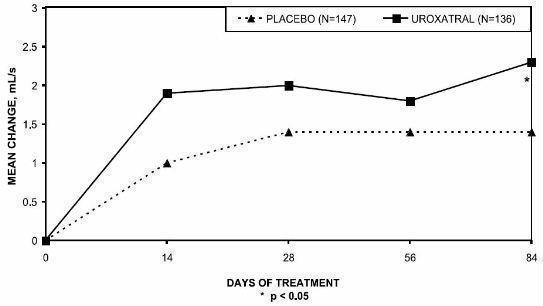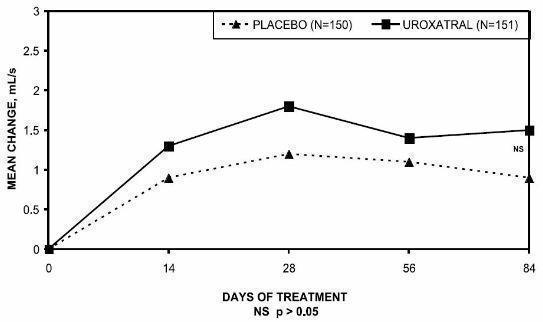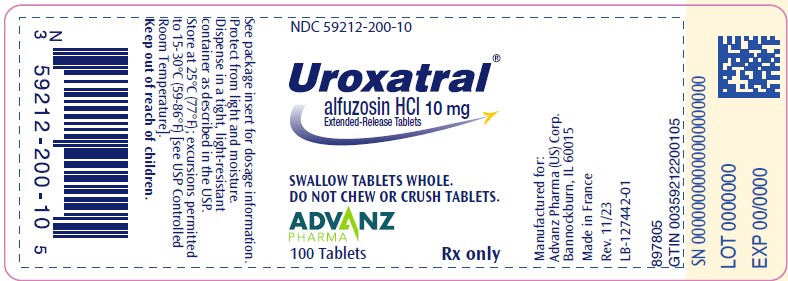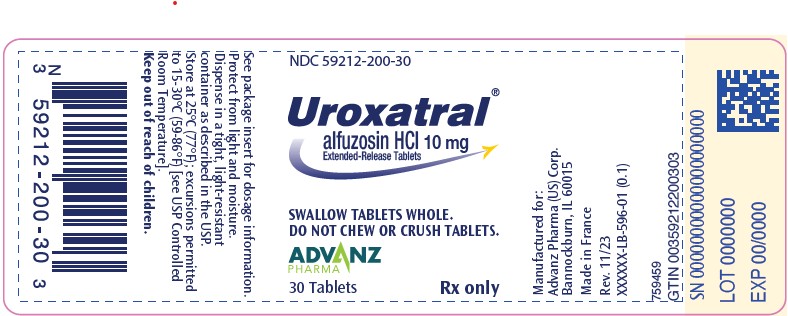 DRUG LABEL: Uroxatral
NDC: 59212-200 | Form: TABLET, EXTENDED RELEASE
Manufacturer: Advanz Pharma (US) Corp.
Category: prescription | Type: Human Prescription Drug Label
Date: 20241205

ACTIVE INGREDIENTS: alfuzosin hydrochloride 10 mg/1 1
INACTIVE INGREDIENTS: silicon dioxide; ethylcellulose (100 mpa.s); hydrogenated castor oil; hypromelloses; magnesium stearate; mannitol; cellulose, microcrystalline; POVIDONE, UNSPECIFIED; ferric oxide yellow

HIGHLIGHTS OF PRESCRIBING INFORMATION

These highlights do not include all the information needed to use UROXATRAL safely and effectively. See full prescribing information for UROXATRAL.
UROXATRAL® (alfuzosin HCl) extended-release tablets
Initial U.S. Approval: 2003

1 INDICATIONS AND USAGE

UROXATRAL is an alpha adrenergic antagonist, indicated for the treatment of signs and symptoms of benign prostatic hyperplasia. (1)

Important Limitations of Use:
UROXATRAL is not indicated for treatment of hypertension. (1.1)
UROXATRAL is not indicated for use in the pediatric population. (1.1, 8.4, 12.3)

2 DOSAGE AND ADMINISTRATION

10 mg once daily with food and with the same meal each day. (2)

Tablets should not be chewed or crushed (2, 12.3)

3 DOSAGE FORMS AND STRENGTHS

Extended-release tablet: 10 mg (3)

4 CONTRAINDICATIONS

- Moderate or severe hepatic impairment (4, 8.7, 12.3)
- Co-administration with potent CYP3A4 inhibitors (e.g. ketoconazole, itraconazole, ritonavir) (4, 5.4, 7.1, 12.3)
- Known hypersensitivity (e.g., urticaria or angioedema) to alfuzosin or any of the ingredients (4, 6.2)

5 WARNINGS AND PRECAUTIONS

- Postural hypotension/syncope: Care should be taken in patients with symptomatic hypotension or who have had a hypotensive response to other medications or are concomitantly treated with antihypertensive medication or nitrates (5.1)
- Use with caution in patients with severe renal impairment (creatinine clearance <30 mL/min) (5.2, 8.6, 12.3)
- Use with caution in patients with mild hepatic impairment (5.3, 8.7, 12.3)
- Should not be used in combination with other alpha adrenergic antagonists (5.4, 7.2)
- Prostate carcinoma should be ruled out prior to treatment (5.5)
- Intraoperative Floppy Iris Syndrome (IFIS) during cataract surgery may require modifications to the surgical technique (5.6)
- Discontinue UROXATRAL if symptoms of angina pectoris appear or worsen (5.8)
- Use with caution in patients with a history of QT prolongation or who are taking medications which prolong the QT interval (5.9, 12.2)

6 ADVERSE REACTIONS

Most common adverse reactions in clinical studies (incidence ≥2% and at a higher incidence than placebo): dizziness, upper respiratory tract infection, headache, fatigue. (6.1)

To report SUSPECTED ADVERSE REACTIONS, contact Advanz Pharma (US) Corp. at 1-877-370-1142 or FDA at 1-800-FDA-1088 or www.fda.gov/medwatch.

7 DRUG INTERACTIONS

- Concomitant use of PDE5 inhibitors with alpha adrenergic antagonists, including UROXATRAL, can potentially cause symptomatic hypotension (5.4, 7.4)

FULL PRESCRIBING INFORMATION

1 INDICATIONS AND USAGE

UROXATRAL is indicated for the treatment of signs and symptoms of benign prostatic hyperplasia.

1.1 Important Limitations of Use

UROXATRAL is not indicated for the treatment of hypertension.
UROXATRAL is not indicated for use in the pediatric population.

2 DOSAGE AND ADMINISTRATION

The recommended dosage is one 10 mg UROXATRAL (alfuzosin HCl) extended-release tablet once daily. The extent of absorption of alfuzosin is 50% lower under fasting conditions. Therefore, Uroxatral should be taken with food and with the same meal each day. The tablets should not be chewed or crushed.

3 DOSAGE FORMS AND STRENGTHS

UROXATRAL (alfuzosin HCl) extended-release tablet 10 mg is available as a round, three-layer tablet: one white layer between two yellow layers, debossed with X10.

4 CONTRAINDICATIONS

UROXATRAL is contraindicated for use:

- in patients with moderate or severe hepatic impairment (Childs-Pugh categories B and C), since alfuzosin blood levels are increased in these patients [see Use in Specific Populations (8.7) and Clinical Pharmacology (12.3)].
- with potent CYP3A4 inhibitors such as ketoconazole, itraconazole, and ritonavir, since alfuzosin blood levels are increased [see Drug Interactions (7.1) and Clinical Pharmacology (12.3)].
- in patients with known hypersensitivity, such as urticaria and angioedema, to alfuzosin hydrochloride or any component of UROXATRAL tablets [see Adverse Reactions (6.2)]

5 WARNINGS AND PRECAUTIONS

5.1 Postural Hypotension

Postural hypotension with or without symptoms (e.g., dizziness) may develop within a few hours following administration of UROXATRAL. As with other alpha adrenergic antagonists, there is a potential for syncope. Patients should be warned of the possible occurrence of such events and should avoid situations where injury could result should syncope occur. There may be an increased risk of hypotension/postural hypotension and syncope when taking UROXATRAL concomitantly with anti-hypertensive medication and nitrates. Care should be taken when UROXATRAL is administered to patients with symptomatic hypotension or patients who have had a hypotensive response to other medications.

5.2 Patients with Renal Impairment

Caution should be exercised when UROXATRAL is administered in patients with severe renal impairment (creatinine clearance < 30 mL/min) [see Use in Specific Populations (8.6) and Clinical Pharmacology (12.3)].

5.3 Patients with Hepatic Impairment

UROXATRAL is contraindicated for use in patients with moderate or severe hepatic impairment [see Contraindications (4), Use in Specific Populations (8.7) and Clinical Pharmacology (12.3)]. Although the pharmacokinetics of UROXATRAL have not been studied in patients with mild hepatic impairment, caution should be exercised when UROXATRAL is administered to such patients [see Use in Specific Populations (8.7) and Clinical Pharmacology (12.3)].

5.4 Drug-Drug Interactions

Potent CYP3A4 Inhibitors: UROXATRAL is contraindicated for use with potent CYP3A4 inhibitors (e.g. ketoconazole, itraconazole, ritonavir) since alfuzosin blood levels are increased [see Contraindications (4), Drug Interactions (7.1) and Clinical Pharmacology (12.3)].

Other alpha adrenergic antagonists: UROXATRAL is an alpha adrenergic antagonist and should not be used in combination with other alpha adrenergic antagonist [see Drug Interactions (7.2)].

Phosphodiesterase-5 (PDE5) Inhibitors: PDE5-inhibitors are also vasodilators. Caution is advised for concomitant use of PDE5-inhibitors and UROXATRAL, as this combination can potentially cause symptomatic hypotension [see Drug Interactions (7.4)].

5.5 Prostatic Carcinoma

Carcinoma of the prostate and benign prostatic hyperplasia (BPH) cause many of the same symptoms. These two diseases frequently coexist. Therefore, patients thought to have BPH should be examined to rule out the presence of carcinoma of the prostate prior to starting treatment with UROXATRAL.

5.6 Intraoperative Floppy Iris Syndrome (IFIS)

IFIS has been observed during cataract surgery in some patients on or previously treated with alpha adrenergic antagonists. This variant of small pupil syndrome is characterized by the combination of a flaccid iris that billows in response to intraoperative irrigation currents, progressive intraoperative miosis despite preoperative dilation with standard mydriatic drugs, and potential prolapse of the iris toward the phacoemulsification incisions. The patient's ophthalmologist should be prepared for possible modifications to their surgical technique, such as the utilization of iris hooks, iris dilator rings, or viscoelastic substances.

There does not appear to be a benefit of stopping alpha adrenergic antagonist therapy prior to cataract surgery.

5.7 Priapism

Rarely (probably less than 1 in 50,000), alfuzosin, like other alpha adrenergic antagonists, has been associated with priapism (persistent painful penile erection unrelated to sexual activity). Because this condition can lead to permanent impotence if not properly treated, patients should be advised about the seriousness of the condition [see Adverse Reactions (6.2) and Patient Counseling Information [17.3]).

5.8 Coronary Insufficiency

If symptoms of angina pectoris should appear or worsen, UROXATRAL should be discontinued.

5.9 Patients with Congenital or Acquired QT Prolongation

Use with caution in patients with acquired or congenital QT prolongation or who are taking medications that prolong the QT interval [see Clinical Pharmacology (12.2)].

6 ADVERSE REACTIONS

6.1 Clinical Trials Experience

Because clinical trials are conducted under widely varying conditions, adverse reaction rates observed in the clinical trials of a drug cannot be directly compared to rates in the clinical trials of another drug and may not reflect the rates observed in clinical practice.

The incidence of adverse reactions has been ascertained from 3 placebo-controlled clinical trials involving 1,608 men where daily doses of 10 and 15 mg alfuzosin were evaluated. In these 3 trials, 473 men received UROXATRAL (alfuzosin HCl) 10 mg extended-release tablets. In these trials, 4% of patients taking UROXATRAL (alfuzosin HCl) 10 mg extended-release tablets withdrew from the trial due to adverse reactions, compared with 3% in the placebo group.

Table 1 summarizes adverse reactions that occurred in ≥2% of patients receiving UROXATRAL, and at a higher incidence than that of the placebo group. In general, the adverse reactions seen in long-term use were similar in type and frequency to the events described below for the 3-month trials.

Table 1 — Adverse Reactions Occurring in ≥2% of UROXATRAL-Treated Patients and More Frequently than with Placebo in 3-Month Placebo-Controlled Clinical Trials
Adverse Reaction | Placebo (n=678) | UROXATRAL (n=473)
Dizziness | 19 (2.8%) | 27 (5.7%)
Upper respiratory tract infection | 4 (0.6%) | 14 (3.0%)
Headache | 12 (1.8%) | 14 (3.0%)
Fatigue | 12 (1.8%) | 13 (2.7%)

The following adverse reactions, reported by between 1% and 2% of patients receiving UROXATRAL and occurring more frequently than with placebo, are listed alphabetically by body system and by decreasing frequency within body system:

Body as a whole: pain

Gastrointestinal system: abdominal pain, dyspepsia, constipation, nausea

Reproductive system: impotence

Respiratory system: bronchitis, sinusitis, pharyngitis

Signs and Symptoms of Orthostasis in Clinical Trials: The adverse reactions related to orthostasis that occurred in the double-blind phase 3 trials with alfuzosin 10 mg are summarized in Table 2. Approximately 20% to 30% of patients in these trials were taking antihypertensive medication.

Table 2— Number (%) of Patients with Symptoms Possibly Associated with Orthostasis in 3-Month Placebo-Controlled Clinical Trials
Symptoms | Placebo (n=678) | UROXATRAL (n=473)
Dizziness | 19 (2.8%) | 27 (5.7%)
Hypotension or postural hypotension | 0 | 2 (0.4%)
Syncope | 0 | 1 (0.2%)

Testing for blood pressure changes or orthostatic hypotension was conducted in three controlled studies. Decreased systolic blood pressure (≤90 mm Hg, with a decrease ≥20 mm Hg from baseline) was observed in none of the 674 placebo patients and 1 (0.2%) of the 469 UROXATRAL patients. Decreased diastolic blood pressure (≤50 mm Hg, with a decrease ≥15 mm Hg from baseline) was observed in 3 (0.4%) of the placebo patients and in 4 (0.9%) of the UROXATRAL patients. A positive orthostatic test (decrease in systolic blood pressure of ≥20 mm Hg upon standing from the supine position) was seen in 52 (7.7%) of placebo patients and in 31 (6.6%) of the UROXATRAL patients.

6.2 Post-Marketing Experience

The following adverse reactions have been identified during post approval use of UROXATRAL. Because these reactions are reported voluntarily from a population of uncertain size, it is not always possible to reliably estimate their frequency or establish a causal relationship to drug exposure.

General disorders: edema

Cardiac disorders: tachycardia, chest pain, angina pectoris in patients with pre-existing coronary artery disease, atrial fibrillation

Gastrointestinal disorders: diarrhea, vomiting

Hepatobiliary disorders: hepatocellular and cholestatic liver injury (including cases with jaundice leading to drug discontinuation)

Respiratory system disorders: rhinitis

Reproductive system disorders: priapism

Skin and subcutaneous tissue disorders: rash, pruritis, urticaria, angioedema, toxic epidermal necrolysis

Vascular disorders: flushing

Blood and lymphatic system disorders: thrombocytopenia

During cataract surgery, a variant of small pupil syndrome known as Intraoperative Floppy Iris Syndrome (IFIS) has been reported in some patients on or previously treated with alpha adrenergic antagonists [see Warnings and Precautions (5.6)].

7 DRUG INTERACTIONS

7.1 CYP3A4 Inhibitors

UROXATRAL is contraindicated for use with potent CYP3A4 inhibitors such as ketoconazole, itraconazole, or ritonavir, since alfuzosin blood levels are increased [see Contraindications (4), Warnings and Precautions (5.4) and Clinical Pharmacology (12.3)].

7.2 Alpha Adrenergic Antagonists

The pharmacokinetic and pharmacodynamic interactions between UROXATRAL and other alpha adrenergic antagonists have not been determined. However, interactions may be expected, and UROXATRAL should not be used in combination with other alpha adrenergic antagonists [see Warnings and Precautions (5.4)].

7.3 Antihypertensive Medication and Nitrates

There may be an increased risk of hypotension/postural hypotension and syncope when taking UROXATRAL concomitantly with anti-hypertensive medication and nitrates [see Warnings and Precautions (5.1)].

7.4 PDE5 Inhibitors

Caution is advised when alpha adrenergic antagonists, including UROXATRAL, are co-administered with PDE5 inhibitors. Alpha adrenergic antagonists and PDE5 inhibitors are both vasodilators that can lower blood pressure. Concomitant use of these two drug classes can potentially cause symptomatic hypotension [see Warnings and Precautions (5.4)].

8 USE IN SPECIFIC POPULATIONS

8.1 Pregnancy

TERATOGENIC EFFECTS

Risk Summary

Uroxatral is not indicated for use in women.
There are no adequate data on the developmental risk associated with use of UROXATRAL in pregnant women.
Based on findings from animal studies, alfuzosin administered during the period of organogenesis was not teratogenic, embryotoxic or fetotoxic at upto 1200 times the MRHD of 10 mg via AUC in rats and 3 times in rabbit, via body surface area.
In the U.S. general population, the estimated background risk of major birth defects and miscarriages in clinically recognized pregnancies is 2 to 4% and 15 to 20% respectively.
Data
Animal data
Alfuzosin was not teratogenic, embryotoxic or fetotoxic in rats at plasma exposure levels (based on AUC of unbound drug) up to 1200 times (maternal oral dose of 250 mg/kg/day) the maximum recommended human dose (MRHD) of 10 mg. In rabbits administered up to 3 times the MRHD (based on body surface area) (maternal oral dose of 100 mg/kg/day) no embryofetal toxicity or teratogenicity was observed. Gestation was slightly prolonged in rats at exposure levels (based on AUC of unbound drug) approximately 12 times (greater than 5 mg/kg/day oral maternal dose) the MRHD, but difficulties with parturition were not observed.

8.2 Lactation

Risk Summary
UROXATRAL is not indicated for use in women. There are no data on presence of UROXATRAL in human milk, the effect on breastfed child, or effect on milk production.

8.4 Pediatric Use

UROXATRAL is not indicated for use in the pediatric population.

Efficacy of alfuzosin hydrochloride was not demonstrated in a randomized, double-blind, placebo-controlled, efficacy and safety trial conducted in 172 patients ages 2 to 16 years with elevated detrusor leak point pressure (LPP≥40 cm H2O) of neurologic origin treated with alfuzosin hydrochloride using pediatric formulations. The trial included a 12-week efficacy phase followed by a 40-week safety extension period. No statistically significant difference in the proportion of patients achieving a detrusor leak point pressure of <40 cm H20 was observed between the alfuzosin and placebo groups.

During the placebo-controlled trial, the adverse reactions reported in ≥2% of patients treated with alfuzosin and at a higher incidence than in the placebo group were: pyrexia, headache, respiratory tract infection, cough, epistaxis and diarrhea. The adverse reactions reported for the whole 12-month trial period, which included the open-label extension, were similar in type and frequency to the reactions observed during the 12-week period.

Alfuzosin hydrochloride was not studied in patients below the age of 2.

8.5 Geriatric Use

Of the total number of subjects in clinical studies of UROXATRAL, 48% were 65 years of age and over, whereas 11% were 75 and over. No overall differences in safety or effectiveness were observed between these subjects and younger subjects, but greater sensitivity of some older individuals cannot be ruled out [see Clinical Pharmacology (12.3)]

8.6 Renal Impairment

Systemic exposure was increased by approximately 50% in pharmacokinetic studies of patients with mild, moderate, and severe renal impairment [see Clinical Pharmacology (12.3)]. In phase 3 studies, the safety profile of patients with mild (n=172) or moderate (n=56) renal impairment was similar to the patients with normal renal function in those studies. Safety data are available in only a limited number of patients (n=6) with creatinine clearance below 30 mL/min; therefore, caution should be exercised when UROXATRAL is administered in patients with severe renal impairment [see Warnings and Precautions (5.2)].

8.7 Hepatic Impairment

The pharmacokinetics of UROXATRAL have not been studied in patients with mild hepatic impairment. UROXATRAL is contraindicated for use in patients with moderate or severe hepatic impairment [see Contraindications (4), Warnings and Precautions (5.3) and Clinical Pharmacology (12.3)].

10 OVERDOSAGE

Should overdose of UROXATRAL lead to hypotension, support of the cardiovascular system is of first importance. Restoration of blood pressure and normalization of heart rate may be accomplished by keeping the patient in the supine position. If this measure is inadequate, then the administration of intravenous fluids should be considered. If necessary, vasopressors should then be used, and the renal function should be monitored and supported as needed. Alfuzosin is 82% to 90% protein bound; therefore, dialysis may not be of benefit.

11 DESCRIPTION

Each UROXATRAL extended-release tablet contains 10 mg alfuzosin hydrochloride as the active ingredient. Alfuzosin hydrochloride is a white to off-white crystalline powder that melts at approximately 240°C. It is freely soluble in water, sparingly soluble in alcohol, and practically insoluble in dichloromethane.

Alfuzosin hydrochloride is (R,S)-N-[3-[(4-amino-6,7-dimethoxy-2-quinazolinyl) methylamino] propyl] tetrahydro-2-furancarboxamide hydrochloride. The empirical formula of alfuzosin hydrochloride is C19H27N5O4•HCl. The molecular weight of alfuzosin hydrochloride is 425.9. Its structural formula is:

The tablet also contains the following inactive ingredients: colloidal silicon dioxide (NF), ethylcellulose (NF), hydrogenated castor oil (NF), hydroxypropyl methylcellulose (USP), magnesium stearate (NF), mannitol (USP), microcrystalline cellulose (NF), povidone (USP), and yellow ferric oxide (NF).

12 CLINICAL PHARMACOLOGY

12.1 Mechanism of Action

Alfuzosin is a selective antagonist of post-synaptic alpha1-adrenoreceptors, which are located in the prostate, bladder base, bladder neck, prostatic capsule, and prostatic urethra.

12.2 Pharmacodynamics

Alfuzosin exhibits selectivity for alpha adrenergic receptors in the lower urinary tract. Blockade of these adrenoreceptors can cause smooth muscle in the bladder neck and prostate to relax, resulting in an improvement in urine flow and a reduction in symptoms of BPH.

Cardiac Electrophysiology
The effect of 10 mg and 40 mg alfuzosin on QT interval was evaluated in a double-blind, randomized, placebo and active-controlled (moxifloxacin 400 mg), 4-way crossover single dose study in 45 healthy white male subjects aged 19 to 45 years. The QT interval was measured at the time of peak alfuzosin plasma concentrations. The 40 mg dose of alfuzosin was chosen because this dose achieves higher blood levels than those achieved with the co-administration of UROXATRAL and ketoconazole 400 mg. Table 3 summarizes the effect on uncorrected QT and mean corrected QT interval (QTc) with different methods of correction (Fridericia, population-specific and subject-specific correction methods) at the time of peak alfuzosin plasma concentrations. No single one of these correction methodologies is known to be more valid. The mean change of heart rate associated with a 10 mg dose of alfuzosin in this study was 5.2 beats/minute and 5.8 beats/minute with 40 mg alfuzosin. The change in heart rate with moxifloxacin was 2.8 beats/minute.

Table 3. Mean QT and QTc changes in msec (95% CI) from baseline at Tmax (relative to placebo) with different methodologies to correct for effect of heart rate.
Drug/Dose | QT | Fridericia method | Population-specific method | Subject-specific method
Alfuzosin 10 mg | -5.8 (-10.2, -1.4) | 4.9 (0.9, 8.8) | 1.8 (-1.4, 5.0) | 1.8 (-1.3, 5.0)
Alfuzosin 40 mg | -4.2 (-8.5, 0.2) | 7.7 (1.9, 13.5) | 4.2 (-0.6, 9.0) | 4.3 (-0.5, 9.2)
Moxifloxacin [Active control] 400 mg | 6.9 (2.3, 11.5) | 12.7 (8.6, 16.8) | 11.0 (7.0, 15.0) | 11.1 (7.2, 15.0)

The QT effect appeared greater for 40 mg compared to 10 mg alfuzosin. The effect of the highest alfuzosin dose (four times the therapeutic dose) studied did not appear as large as that of the active control moxifloxacin at its therapeutic dose. This study, however, was not designed to make direct statistical comparisons between the drugs or the dose levels. There has been no signal of Torsade de Pointes in the extensive post-marketing experience with alfuzosin outside the United States.

A separate post-marketing QT study evaluated the effect of the co-administration of 10 mg alfuzosin with a drug of similar QT effect size. In this study, the mean placebo-subtracted QTcF increase of alfuzosin 10 mg alone was 1.9 msec (upperbound 95% CI, 5.5 msec). The concomitant administration of the two drugs showed an increased QT effect when compared with either drug alone. This QTcF increase [5.9 msec (UB 95% CI, 9.4 msec)] was not more than additive. Although this study was not designed to make direct statistical comparisons between drugs, the QT increase with both drugs given together appeared to be lower than the QTcF increase seen with the positive control moxifloxacin 400 mg [10.2 msec (UB 95% CI, 13.8 msec)]. The clinical impact of these QTc changes is unknown.

12.3 Pharmacokinetics

The pharmacokinetics of UROXATRAL have been evaluated in adult healthy male volunteers after single and/or multiple administration with daily doses ranging from 7.5 mg to 30 mg, and in patients with BPH at doses from 7.5 mg to 15 mg.

Absorption
The absolute bioavailability of UROXATRAL 10 mg tablets under fed conditions is 49%. Following multiple dosing of 10 mg UROXATRAL under fed conditions, the time to maximum concentration is 8 hours. Cmax and AUC0–24 are 13.6 (SD = 5.6) ng/mL and 194 (SD = 75) ng∙h/mL, respectively. UROXATRAL exhibits linear kinetics following single and multiple dosing up to 30 mg. Steady-state plasma levels are reached with the second dose of UROXATRAL administration. Steady-state alfuzosin plasma concentrations are 1.2- to 1.6-fold higher than those observed after a single administration.

Effect of Foods
As illustrated in Figure 1, the extent of absorption is 50% lower under fasting conditions. Therefore, UROXATRAL should be taken with food and with the same meal each day [see Dosage and Administration (2)].

Figure 1 - Mean (SEM) Alfuzosin Plasma Concentration-Time Profiles after a Single Administration of UROXATRAL 10 mg tablets to 8 Healthy Middle-Aged Male Volunteers in Fed and Fasted States

Distribution
The volume of distribution following intravenous administration in healthy male middle-aged volunteers was 3.2 L/kg. Results of in vitro studies indicate that alfuzosin is moderately bound to human plasma proteins (82% to 90%), with linear binding over a wide concentration range (5 to 5,000 ng/mL).

Metabolism
Alfuzosin undergoes extensive metabolism by the liver, with only 11% of the administered dose excreted unchanged in the urine. Alfuzosin is metabolized by three metabolic pathways: oxidation, O-demethylation, and N-dealkylation. The metabolites are not pharmacologically active. CYP3A4 is the principal hepatic enzyme isoform involved in its metabolism.

Excretion
Following oral administration of ^14C-labeled alfuzosin solution, the recovery of radioactivity after 7 days (expressed as a percentage of the administered dose) was 69% in feces and 24% in urine. Following oral administration of UROXATRAL 10 mg tablets, the apparent elimination half-life is 10 hours.

Specific Populations

Geriatric Use: In a pharmacokinetic assessment during phase 3 clinical studies in patients with BPH, there was no relationship between peak plasma concentrations of alfuzosin and age. However, trough levels were positively correlated with age. The concentrations in subjects ≥75 years of age were approximately 35% greater than in those below 65 years of age.

Renal Impairment: The Pharmacokinetic profiles of UROXATRAL 10 mg tablets in subjects with normal renal function (CLCR>80 mL/min), mild impairment (CLCR 60 to 80 mL/min), moderate impairment (CLCR 30 to 59 mL/min), and severe impairment (CLCR <30 mL/min) were compared. These clearances were calculated by the Cockcroft-Gault formula. Relative to subjects with normal renal function, the mean Cmax and AUC values were increased by approximately 50% in patients with mild, moderate, or severe renal impairment [see Warnings and Precautions (5.2) and Use in Specific Populations (8.6)].

Hepatic Impairment: The pharmacokinetics of UROXATRAL have not been studied in patients with mild hepatic impairment. In patients with moderate or severe hepatic insufficiency (Child-Pugh categories B and C), the plasma apparent clearance (CL/F) was reduced to approximately one-third to one-fourth that observed in healthy subjects. This reduction in clearance results in three to four-fold higher plasma concentrations of alfuzosin in these patients compared to healthy subjects. Therefore, UROXATRAL is contraindicated in patients with moderate to severe hepatic impairment [see Contraindications (4), Warnings and Precautions (5.3) and Use in Specific Populations (8.7)].

PEDIATRIC USE

Pediatric Use: UROXATRAL tablets are not indicated for use in the pediatric population [see Indications and Usage (1.1) and Use in Specific Populations (8.4)].

Drug-Drug Interactions

Metabolic Interactions
CYP3A4 is the principal hepatic enzyme isoform involved in the metabolism of alfuzosin.

Potent CYP3A4 Inhibitors
Repeated oral administration of 400 mg/day of ketoconazole, a potent inhibitor of CYP3A4, increased alfuzosin Cmax by 2.3-fold and AUClast by 3.2-fold, following a single 10 mg dose of alfuzosin.

In another study, repeated oral administration of a lower (200 mg/day) dose of ketoconazole increased alfuzosin Cmax by 2.1-fold and AUClast by 2.5-fold, following a single 10 mg dose of alfuzosin.

Therefore, UROXATRAL is contraindicated for co-administration with potent inhibitors of CYP3A4 (e.g., ketoconazole, itraconazole, or ritonavir) because of increased alfuzosin exposure[see Contraindications (4), Warnings and Precautions (5.4) and Drug Interactions (7.1)].

Moderate CYP3A4 Inhibitors
Diltiazem: Repeated co-administration of 240 mg/day of diltiazem, a moderately-potent inhibitor of CYP3A4, with 7.5 mg/day (2.5 mg three times daily) alfuzosin (equivalent to the exposure with UROXATRAL) increased the Cmax and AUC0–24 of alfuzosin 1.5- and 1.3-fold, respectively. Alfuzosin increased the Cmax and AUC0–12 of diltiazem 1.4-fold. Although no changes in blood pressure were observed in this study, diltiazem is an antihypertensive medication and the combination of UROXATRAL and antihypertensive medications has the potential to cause hypotension in some patients [see Warnings and Precautions (5.1)].

In human liver microsomes, at concentrations that are achieved at the therapeutic dose, alfuzosin did not inhibit CYP1A2, 2A6, 2C9, 2C19, 2D6 or 3A4 isoenzymes. In primary culture of human hepatocytes, alfuzosin did not induce CYP1A, 2A6 or 3A4 isoenzymes.

Other Interactions
Warfarin: Multiple dose administration of an immediate release tablet formulation of alfuzosin 5 mg twice daily for six days to six healthy male volunteers did not affect the pharmacological response to a single 25 mg oral dose of warfarin.

Digoxin: Repeated co-administration of UROXATRAL 10 mg tablets and digoxin 0.25 mg/day for 7 days did not influence the steady-state pharmacokinetics of either drug.

Cimetidine: Repeated administration of 1 g/day cimetidine increased both alfuzosin Cmax and AUC values by 20%.

Atenolol: Single administration of 100 mg atenolol with a single dose of 2.5 mg of an immediate release alfuzosin tablet in eight healthy young male volunteers increased alfuzosin Cmax and AUC values by 28% and 21%, respectively. Alfuzosin increased atenolol Cmax and AUC values by 26% and 14%, respectively. In this study, the combination of alfuzosin with atenolol caused significant reductions in mean blood pressure and in mean heart rate. [see Warnings and Precautions (5.1)].

Hydrochlorothiazide: Single administration of 25 mg hydrochlorothiazide did not modify the pharmacokinetic parameters of alfuzosin. There was no evidence of pharmacodynamic interaction between alfuzosin and hydrochlorothiazide in the 8 patients in this study.

13 NONCLINICAL TOXICOLOGY

13.1 Carcinogenesis, Mutagenesis, Impairment of Fertility

There was no evidence of a drug-related increase in the incidence of tumors in mice following dietary administration of 100 mg/kg/day alfuzosin for 98 weeks (13 and 15 times the maximum recommended human dose [MRHD] of 10 mg based on AUC of unbound drug), in females and males, respectively. The highest dose tested in female mice may not have constituted a maximally tolerated dose. Likewise, there was no evidence of a drug-related increase in the incidence of tumors in rats following dietary administration of 100 mg/kg/day alfuzosin for 104 weeks (53 and 37 times the MRHD in females and males, respectively).

Alfuzosin showed no evidence of mutagenic effect in the Ames and mouse lymphoma assays, and was free of any clastogenic effects in the Chinese hamster ovary cell and in vivo mouse micronucleus assays. Alfuzosin treatment did not induce DNA repair in a human cell line.

There was no evidence of reproductive organ toxicity when male rats were administered oral doses of several hundred times (250 mg/kg/day for 26 weeks) the MRHD of alfuzosin. No impairment of fertility was observed following oral (gavage) administration to male rats at doses of up to 125 mg/kg/day for 70 days. Estrous cycling was inhibited in rats and dogs at approximately 12 and 18 times the MRHD respectively (doses of 25 mg/kg and 20 mg/kg, respectively), but did not result in impaired fertility in female rats.

14 CLINICAL STUDIES

Three randomized placebo-controlled, double-blind, parallel-arm, 12-week trials were conducted with the 10 mg daily dose of alfuzosin. In these three trials, 1,608 patients [mean age 64.2 years, range 49–92 years; Caucasian (96.1%), Black (1.6%), Asian (1.1%), Other (1.2%)] were randomized and 473 patients received UROXATRAL 10 mg daily. Table 4 provides the results of the three trials that evaluated the 10 mg dose.

There were two primary efficacy variables in these three studies. The International Prostate Symptom Score (IPSS, or AUA Symptom Score) consists of seven questions that assess the severity of both irritative (frequency, urgency, nocturia) and obstructive (incomplete emptying, stopping and starting, weak stream, and pushing or straining) symptoms, with possible scores ranging from 0 to 35 with higher numerical scores on the IPSS total symptom score representing greater severity of symptoms. The second efficacy variable was peak urinary flow rate. The peak flow rate was measured just prior to the next dose in study 2 and on average at 16 hours post-dosing in trials 1 and 3.
There was a statistically significant reduction from baseline to last assessment (Week 12) in the IPSS total symptom score versus placebo in all three studies, indicating a reduction in symptom severity (Table 5 and Figures 2, 3, and 4).
Table 4 - Mean Change (SD) from Baseline to week 12 in International Prostate Symptom Score in Three Randomized, Controlled, Double Blind Trials

Symptom Score | Trial 1 |  | Trial 2 |  | Trial 3
Symptom Score | Placebo (n=167) | UROXATRAL 10 mg (n=170) | Placebo (n=152) | UROXATRAL 10 mg (n=137) | Placebo (n=150) | UROXATRAL 10 mg (n=151)
Total symptom score
Baseline | 18.2 (6.4) | 18.2 (6.3) | 17.7 (4.1) | 17.3 (3.5) | 17.7 (5.0) | 18.0 (5.4)
Change [Difference between baseline and week 12.] | -1.6 (5.8) | -3.6 (4.8) | -4.9 (5.9) | -6.9 (4.9) | -4.6 (5.8) | -6.5 (5.2)
p-value | 0.001 |  | 0.002 |  | 0.007

Figure 2 — Mean Change from Baseline in IPSS Total Symptom Score: Trial 1

Figure 3 — Mean Change from Baseline in IPSS Total Symptom Score: Trial 2

Figure 4 — Mean Change from Baseline in IPSS Total Symptom Score: Trial 3

Peak urinary flow rate was increased statistically significantly from baseline to last assessment (Week 12) versus placebo in trials 1 and 2 (Table 5 and Figures 5, 6, and 7).

Table 5 — Mean (SD) Change from Baseline to Week 12 in Peak Urine Flow Rate (mL/sec) in Three Randomized, Controlled, Double-Blind Trials
 | Trial 1 |  | Trial 2 |  | Trial 3
 | Placebo (n=167) | UROXATRAL 10 mg (n=170) | Placebo (n=147) | UROXATRAL 10 mg (n=136) | Placebo (n=150) | UROXATRAL 10 mg (n=151)
Mean Peak flow rate
Baseline | 10.2 (4.0) | 9.9 (3.9) | 9.2 (2.0) | 9.4 (1.9) | 9.3 (2.6) | 9.5 (3.0)
Change [Difference between baseline and week 12.] | 0.2 (3.5) | 1.7 (4.2) | 1.4 (3.2) | 2.3 (3.6) | 0.9 (3.0) | 1.5 (3.3)
p-value | 0.0004 |  | 0.03 |  | 0.22

Figure 5 — Mean Change from Baseline in Peak Urine Flow Rate (mL/s): Trial 1

Figure 6 — Mean Change from Baseline in Peak Urine Flow Rate (mL/s): Trial 2

Figure 7 — Mean Change from Baseline in Peak Urine Flow Rate (mL/s): Trial 3

Mean total IPSS decreased at the first scheduled observation at Day 28 and mean peak flow rate increased starting at the first scheduled observation at Day 14 in trials 2 and 3 and Day 28 in trial 1.

16 HOW SUPPLIED/STORAGE AND HANDLING

UROXATRAL is supplied as follows:

Package NDC Number
Bottles of 100 with child-resistant closure, NDC 59212-200-10
Bottles of 30 with child-resistant closure, NDC 59212-200-30

UROXATRAL (alfuzosin HCl) extended-release tablet 10 mg is available as a round, three-layer tablet: one white layer between two yellow layers, debossed with X10.

STORAGE AND HANDLING

Store at 25°C (77°F); excursions permitted to 15° to 30°C (59° to 86°F) [see USP Controlled Room Temperature]. Dispense in a tight, light-resistant container as described in the USP.

Protect from light and moisture.

Keep UROXATRAL out of reach of children.

17 PATIENT COUNSELING INFORMATION

See FDA-approved patient labeling.

17.1 Hypotension/Syncope

Patients should be told about the possible occurrence of symptoms related to postural hypotension, such as dizziness, when beginning UROXATRAL, and they should be cautioned about driving, operating machinery, or performing hazardous tasks during this period. This is important for those with low blood pressure or who are taking antihypertensive medications or nitrates [see Warnings and Precautions (5.1)].

17.2 Intraoperative Floppy Iris Syndrome

Patients should be instructed to tell their ophthalmologist about their use of UROXATRAL before cataract surgery or other procedures involving the eyes, even if the patient is no longer taking UROXATRAL [see Warnings and Precautions (5.6)].

17.3 Priapism

Patients should be advised about the possibility of priapism resulting from treatment with UROXATRAL and medications in the same class. Although this reaction is extremely rare, but if not brought to immediate medical attention, can lead to permanent erectile dysfunction (impotence) [see Warnings and Precautions (5.7)].

17.4 Instructions of Use

UROXATRAL should be taken with food and with the same meal each day.
Patients should be advised not to crush or chew UROXATRAL tablets.

Manufactured for:
Advanz Pharma (US) Corp.
Bannockburn, IL 60015
UROXATRAL® is a registered trademark of Mercury Pharma Group Limited. Distributed by Advanz Pharma (US) Corp. under license.

PATIENT INFORMATION
UROXATRAL® (yoo-ROX-uh-trahl)
(Alfuzosin hydrochloride extended-release tablets)

Read the Patient Information that comes with UROXATRAL before you start using it and each time you get a refill. There may be new information. This leaflet does not take the place of talking with your doctor about your condition or your treatment. You and your doctor should talk about all your medicines, including UROXATRAL, now and at your regular checkups.

What is the most important information I should know about UROXATRAL?

UROXATRAL can cause serious side effects, including a sudden drop in blood pressure, especially when you start treatment. This may cause you to faint, or to feel dizzy or lightheaded.

- Your risk of having this problem may be increased if you take UROXATRAL with certain other medicine that lowers blood pressure:
  - medicines for high blood pressure
  - a nitrate medicine for angina
  Ask your doctor if you are not sure if you are taking one of these medicines.
- Do not drive, operate machinery, or do any dangerous activities until you know how UROXATRAL affects you. This is especially important if you already have a problem with low blood pressure or take medicines to treat high blood pressure.
- If you begin to feel dizzy or lightheaded, lie down with your legs and feet up. If your symptoms do not improve call your doctor.

See the section "What are the possible side effects of UROXATRAL?" for more information about side effects.

What is UROXATRAL?

UROXATRAL is a prescription medicine that is called an "alpha-blocker". UROXATRAL is used in adult men to treat the symptoms of benign prostatic hyperplasia (BPH). UROXATRAL may help to relax the muscles in the prostate and the bladder which may lessen the symptoms of BPH and improve urine flow.

Before prescribing UROXATRAL, your doctor may examine your prostate gland and do a blood test called a prostate specific antigen (PSA) test to check for prostate cancer. Prostate cancer and BPH can cause the same symptoms. Prostate cancer needs a different treatment.

UROXATRAL is not for use in women or children.

Some medicines called "alpha-blockers" are used to treat high blood pressure. UROXATRAL is not for the treatment of high blood pressure.

Who should not take UROXATRAL?

Do not take UROXATRAL if you:

- have certain liver problems
- take antifungal medicines like ketoconazole or itraconazole (Sporanox)
- take anti-HIV medicines like ritonavir (Norvir, Kaletra)
- are allergic to alfuzosin hydrochloride or any of the ingredients in UROXATRAL.
  See the end of this leaflet for a complete list of ingredients in UROXATRAL.

Before taking UROXATRAL, tell your doctor if you:

- have liver problems
- have kidney problems
- have had low blood pressure, especially after taking another medicine. Signs of low blood pressure are fainting, dizziness, and lightheadedness.
- have a heart problem called angina
- or any family members have a rare heart condition known as congenital prolongation of the QT interval.

Tell your doctor about all the medicines you take, including prescription and non-prescription medicines, vitamins and herbal supplements. Some of your other medicines may affect the way UROXATRAL works and cause serious side effects. See "What is the most important information I should know about UROXATRAL?"

Especially tell your doctor if you take:

- another alpha blocker medicine
- a medicine to treat high blood pressure
- a medicine to treat angina
- a medicine to treat erectile dysfunction (ED)
- the antifungal medicines like ketoconazole or itraconazole (Sporanox)
- the anti-HIV medicine like ritonavir (Norvir, Kaletra)

Ask your doctor or pharmacist if you are not sure if your medicine is one of those listed above.

What you need to know while taking UROXATRAL (alfuzosin HCl) tablets

- If you have an eye surgery for cataract (clouding of the eye) planned, tell your ophthalmologist that you are using UROXATRAL or have previously been treated with an alpha-blocker.

How do I take UROXATRAL?

- UROXATRAL comes in child-resistant package.
- Take UROXATRAL exactly as your doctor prescribes it.
- Take UROXATRAL after the same meal each day. Do not take it on an empty stomach.
- Swallow the UROXATRAL tablet whole. Do not crush, split, or chew UROXATRAL tablets.
- If you take too much UROXATRAL call your local poison control center or emergency room right away.

What are the possible side effects of UROXATRAL?

UROXATRAL can cause serious side effects, including:

- See "What is the most important information I should know about UROXATRAL?"
- A painful erection that will not go away. UROXATRAL can cause a painful erection (priapism), which cannot be relieved by having sex. If this happens, get medical help right away. If priapism is not treated, you may not be able to get an erection in the future.

The most common side effects with UROXATRAL are:

- dizziness
- headache
- tiredness

Call your doctor if you get any side effect that bothers you.

These are not all the side effects of UROXATRAL. For more information ask your doctor or pharmacist.

Call your doctor for medical advice about side effects. You may report side effects to FDA at 1-800-FDA-1088.

How do I store UROXATRAL?

- Store UROXATRAL between 59°F and 86°F (15°C and 30°C).
- Protect from light and moisture.

Keep UROXATRAL and all medicines out of the reach of children.

General information about UROXATRAL:

Medicines are sometimes prescribed for conditions that are not mentioned in patient information leaflets. Do not use UROXATRAL for a condition for which it was not prescribed. Do not give UROXATRAL to other people, even if they have the same symptoms you have. It may harm them.

This leaflet summarizes the most important information about UROXATRAL. If you would like more information, talk with your doctor. You can ask your doctor or pharmacist for information about UROXATRAL that is written for health professionals.

What are the ingredients of UROXATRAL?

Active Ingredient: alfuzosin hydrochloride

Inactive Ingredients: colloidal silicon dioxide (NF), ethylcellulose (NF), hydrogenated castor oil (NF), hydroxypropyl methylcellulose (USP), magnesium stearate (NF), mannitol (USP), microcrystalline cellulose (NF), povidone (USP), and yellow ferric oxide (NF).

Manufactured for:
Advanz Pharma (US) Corp.
Bannockburn, IL 60015
UROXATRAL® is a registered trademark of Mercury Pharma Group Limited. Distributed by Advanz Pharma (US) Corp. under license.

PRINCIPAL DISPLAY PANEL - 30 TABLETS BOTTLE

NDC 59212-200-30

Uroxatral®
alfuzosin HCl 10 mg
Extended-Release Tablets

SWALLOW TABLET WHOLE.
DO NOT CHEW OR CRUSH TABLETS.
ADVANZ PHARMA
30 Tablets Rx only

PRINCIPAL DISPLAY PANEL - 100 TABLETS BOTTLE

NDC 59212-200-10

Uroxatral®
alfuzosin HCl 10 mg
Extended-Release Tablets
SWALLOW TABLET WHOLE.
DO NOT CHEW OR CRUSH TABLETS.
ADVANZ PHARMA
100 Tablets Rx only